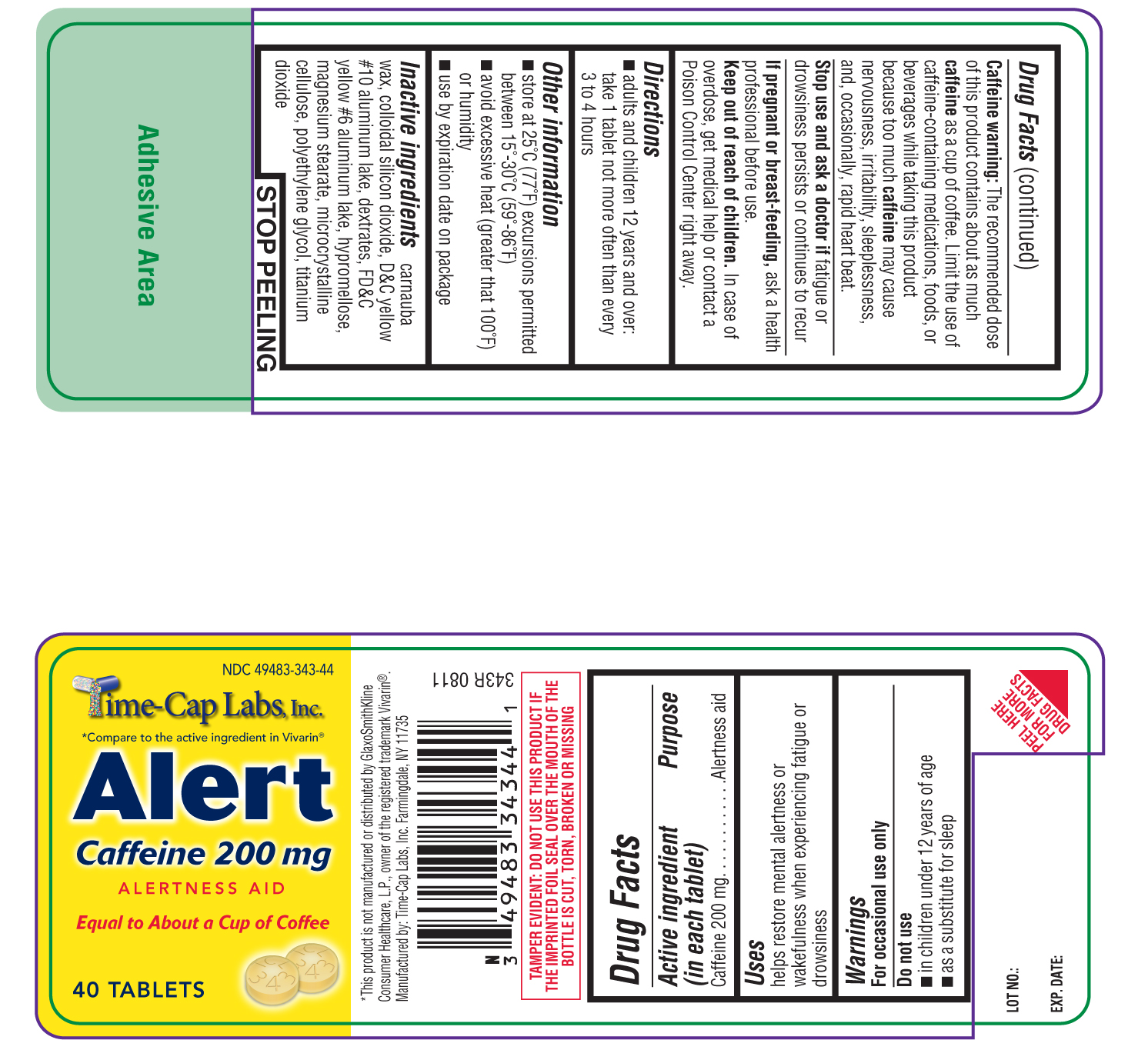 DRUG LABEL: Alert
NDC: 49483-343 | Form: TABLET, FILM COATED
Manufacturer: Time Cap Labs, Inc
Category: otc | Type: HUMAN OTC DRUG LABEL
Date: 20181217

ACTIVE INGREDIENTS: CAFFEINE 200 mg/1 1
INACTIVE INGREDIENTS: CARNAUBA WAX; SILICON DIOXIDE; D&C YELLOW NO. 10; DEXTRATES; FD&C YELLOW NO. 6; HYPROMELLOSE 2910 (6 MPA.S); HYPROMELLOSE 2910 (15 MPA.S); MAGNESIUM STEARATE; CELLULOSE, MICROCRYSTALLINE; POLYETHYLENE GLYCOL 8000; TITANIUM DIOXIDE

343R- ALERT

Active ingredient (in each tablet)

Caffeine 200 mg

Purpose

Alertness aid

Uses

helps restore mental alertness or wakefulness when experiencing fatigue or drowsiness

Warnings
For occasional use only

DO NOT USE

-
  Do not use
  - in children under 12 years of age
  - as a substitute for sleep

OTHER SAFETY INFORMATION

Caffeine warning:

The recommended dose of this product contains about as much

caffeine

as a cup of coffee. Limit the use of caffeine-containing medications, foods, or beverages while taking this product because too much

caffeine

may cause nervousness, irritability, sleeplessness, and, occasionally, rapid heartbeat.

Stop use and ask a doctor if

fatigue or drowsiness persists or continues to recur

If pregnant or breast-feeding,

ask a health professional before use.

Keep out of reach of children.

In case of overdose, get medical help or contact a Poison Control Center right away.

Directions

- adults and children 12 years and over: take 1 tablet not more often than every 3 to 4 hours

Other information

- store at 25°C (77°F) excursions permitted between 15°-30°C (59°-86°F)
- avoid excessive heat (greater than 100°F) or humidity
- use by expiration date on package

Inactive ingredients

carnauba wax, colloidal silicon dioxide, D-C yellow #10 aluminum lake, dextrates, FD-C yellow #6 aluminum lake, hypromellose, magnesium stearate, microcrystalline cellulose, polyethylene glycol, titanium dioxide